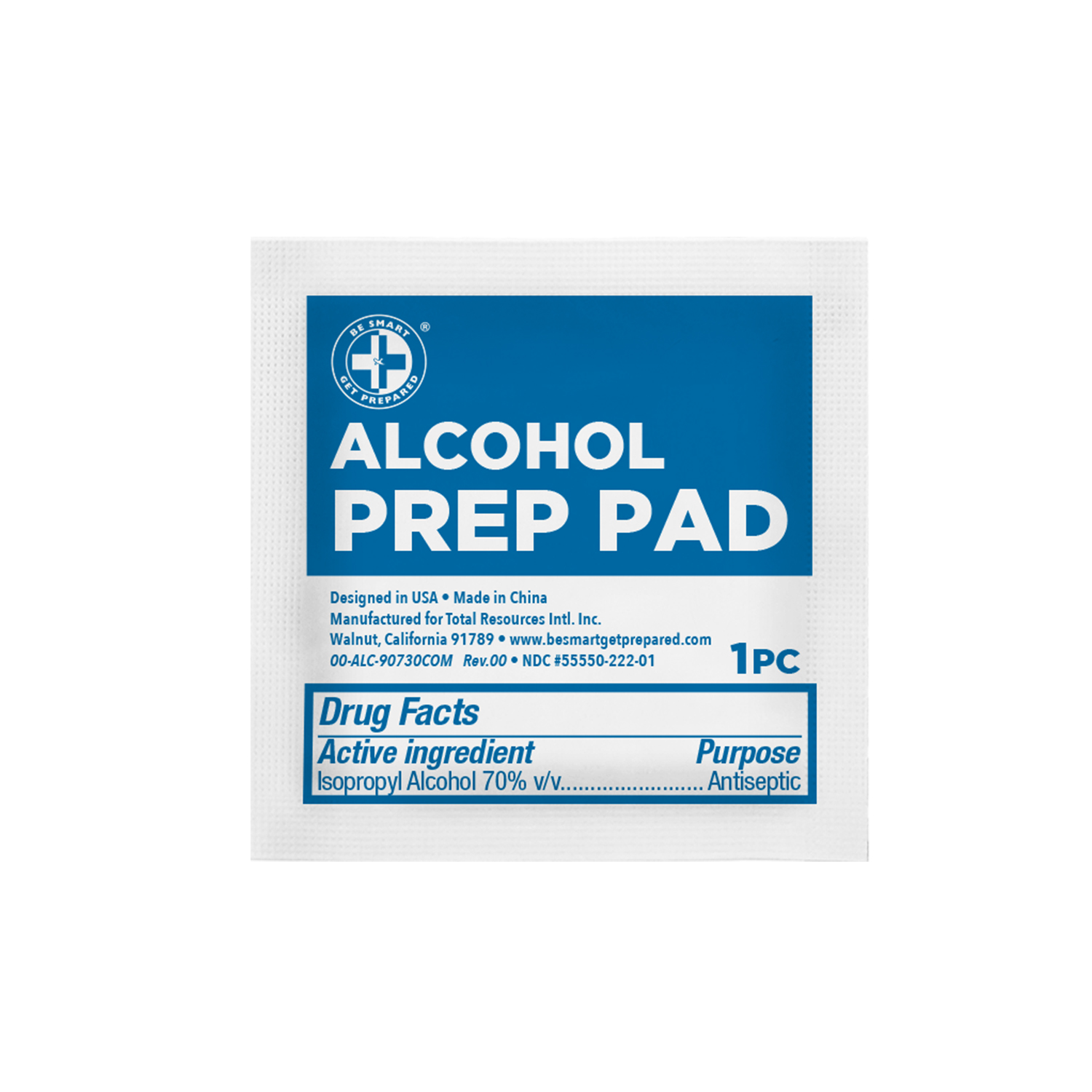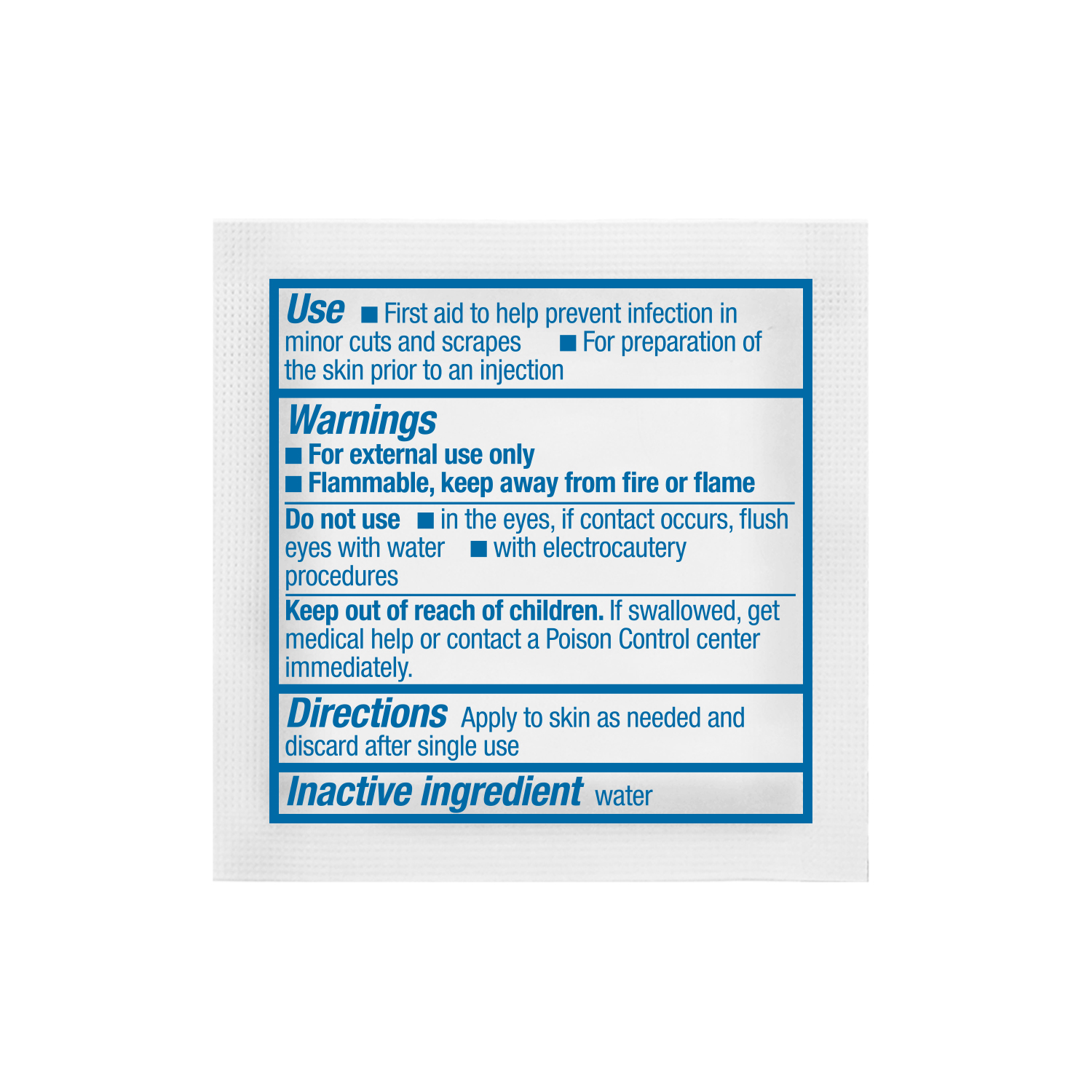 DRUG LABEL: STERILE ALCOHOL PREP PADS
NDC: 55550-222 | Form: SWAB
Manufacturer: Total Resources International Inc.
Category: otc | Type: HUMAN OTC DRUG LABEL
Date: 20251009

ACTIVE INGREDIENTS: ISOPROPYL ALCOHOL 0.7 mL/1 mL
INACTIVE INGREDIENTS: WATER

Sterile Alcohol Prep Pad

Active Ingredients

Isopropyl Alcohol 70% v/v

Purpose

Antiseptic

Use

- First aid to help prevent infection in minor cuts and scrapes
- For preparation of the skin prior to an injection

Warnings

- For external use only
- Flammable, keep away from fire or flame

Do Not Use

- in the eyes, If contact occurs, flush eyes with water
- with electrocautery procedures

Keep out of reach of children

If swallowed, get medical help or contact a Poison Control Center Immediately.

Directions

Apply to skin as needed and discard after single use

Inactive Ingredient

water

DOSAGE AND ADMINISTRATION

Alcohol Prep Pad

1 Pad

Manufactured by: Total Resources International Inc.

Walnut, California 91789

Made in China

REORDER NO: 00-ALC-90730COM